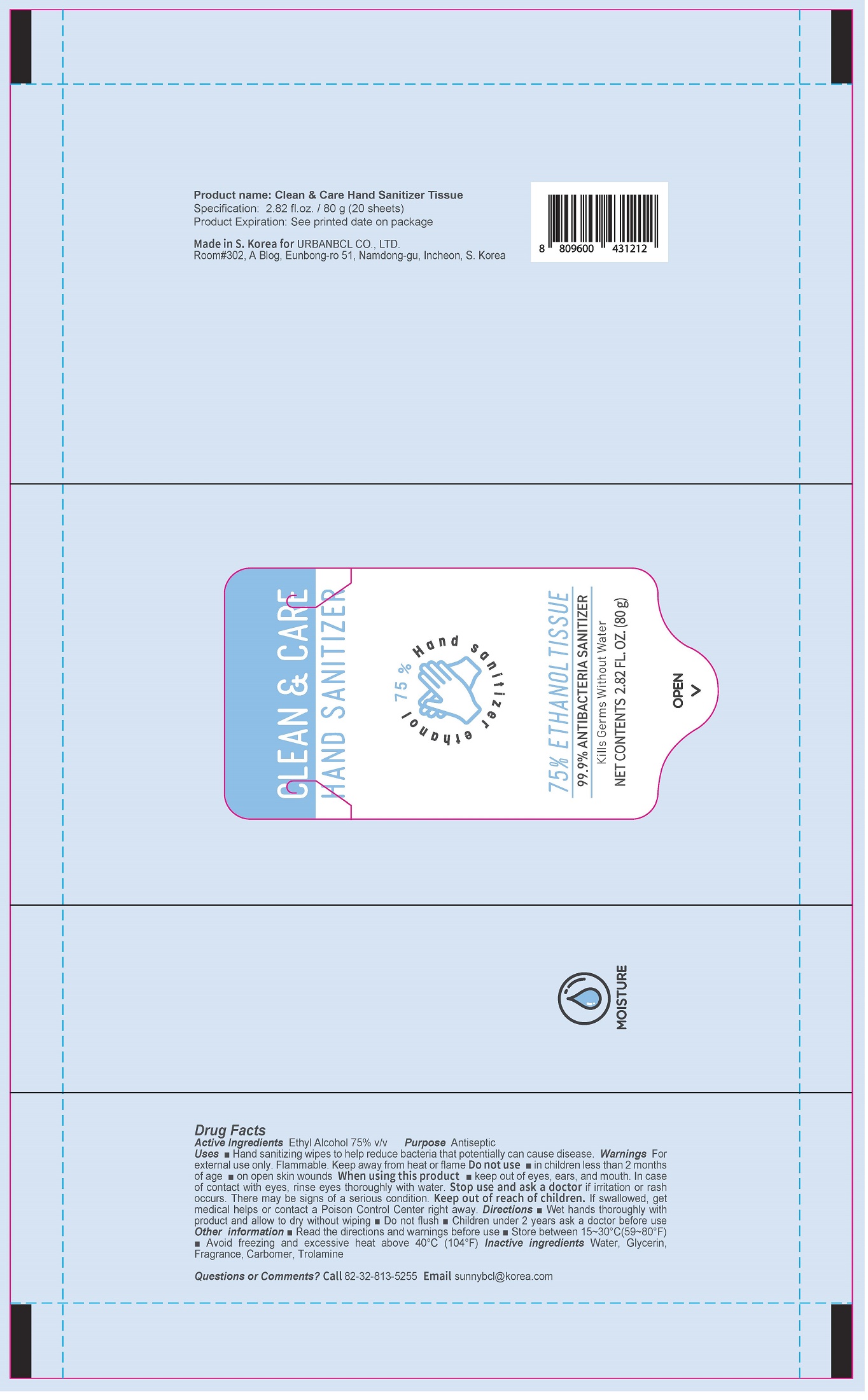 DRUG LABEL: Clean Care Hand Sanitizer Tissue
NDC: 74200-0030 | Form: LIQUID
Manufacturer: URBANBCL CO LTD
Category: otc | Type: HUMAN OTC DRUG LABEL
Date: 20200628

ACTIVE INGREDIENTS: ALCOHOL 75 mL/100 g
INACTIVE INGREDIENTS: TROLAMINE; WATER; GLYCERIN; CARBOMER 940

Drug Facts

ACTIVE INGREDIENT

ethyl alcohol

PURPOSE

to decrease bacteria on the skin that could cause disease

recommended for repeated use

KEEP OUT OF REACH OF THE CHILDREN

WARNINGS

■ Flammable. Keep away from fire or flame.

■ For external use only.

■ Do not use in eyes.

■ lf swallowed, get medical help promptly.

■ Stop use, ask doctor lf irritation occurs.

■ Keep out of reach of children.

DOSAGE AND ADMINISTRATION

for external use only

INACTIVE INGREDIENT

Water, Glycerin, Fragrance, Carbomer, Trolamine

INDICATIONS AND USAGE

■ Wet hands thoroughly with product and allow to dry without wiping

■ Do not flush

■ Children under 2 years ask a doctor before use